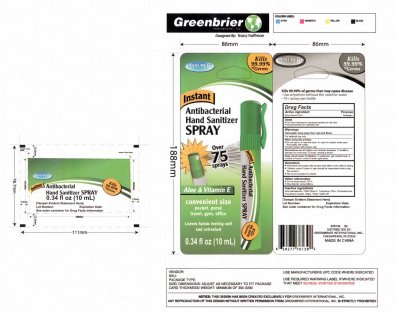 DRUG LABEL: Assured Instant Hand Sanitizer
NDC: 33992-4250 | Form: SPRAY
Manufacturer: Greenbrier International, Inc.
Category: otc | Type: HUMAN OTC DRUG LABEL
Date: 20160928

ACTIVE INGREDIENTS: ALCOHOL 62 mL/100 mL
INACTIVE INGREDIENTS: ALOE VERA LEAF; FD&C BLUE NO. 1; DIMETHICONE; ALPHA-TOCOPHEROL ACETATE; WATER; FD&C YELLOW NO. 5

Assured Instant Hand Sanitizer Spray

Drug Facts

Active Ingredient Purpose

Ethyl Alcohol 62 percent Antiseptic

Uses

For hand washing to decrease bacteria on the skin

Recommended for repeated use

Warnings

Flammable. Keep away from heat and flame.

For external use only.

STOP USE

Discontinue use if irritation and redness develops. If condition persists for more than 72 hours consult a doctor.

Keep out of reach of children. If swallowed, get medical help or contact a Poison Control Center right away.

Directions

Wet hands thoroughly with product and allow to dry without wiping

Children under 6 years of age should be supervised when using this product

Not recommended for infants

Other information

Do not store above 105 degrees F

May discolor some fabrics

INACTIVE INGREDIENT

Aloe barbadensis, FD and C Blue 1 , Fragrance , PEG 18 Dimethicone,

Tocopheryl Acetate, Water, FD and C Yellow 5

DESCRIPTION

Tamper Evident Statement Here

Lot Number: Expiration Date:

See outer container for Drug Facts Information

976139 92

DISTRIBUTED BY:

GREENBRIER INTERNATIONAL, INC.

Chesapeake , VA 23320

MADE IN CHINA

INDICATIONS AND USAGE

Kills 99.99 percent of Germs that may cause disease

Use anywhere without the need for water

75 plus sprays per bottle

OTHER SAFETY INFORMATION

ASSURED

Kills 99.99 percent of Germs

Instant Hand Sanitizer Spray

Over 75 sprays

Aloe and Vitamin E

convenient size

pocket, purse , travel , gym , office

Leaves hands feeling soft and refreshed
0.34 fl oz
10mL